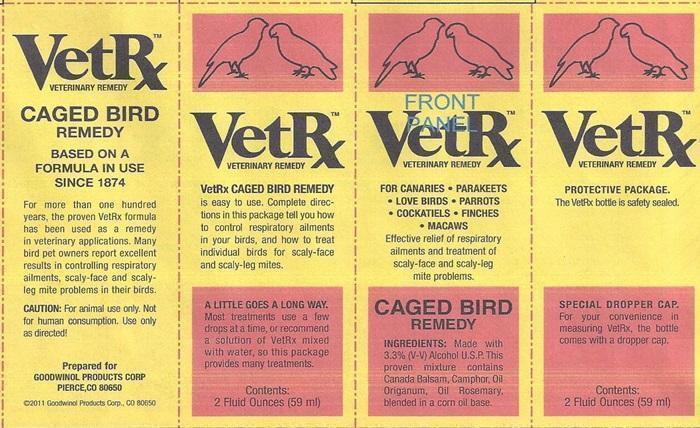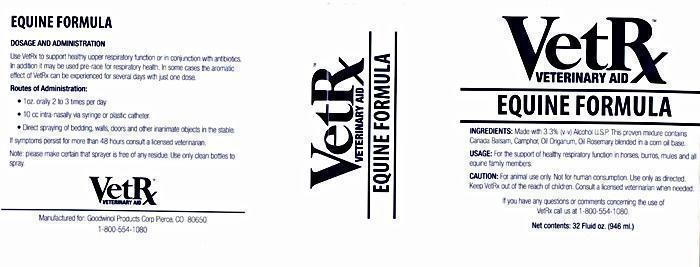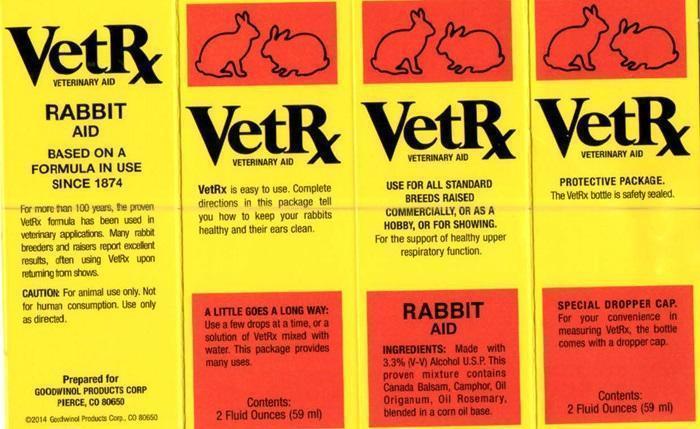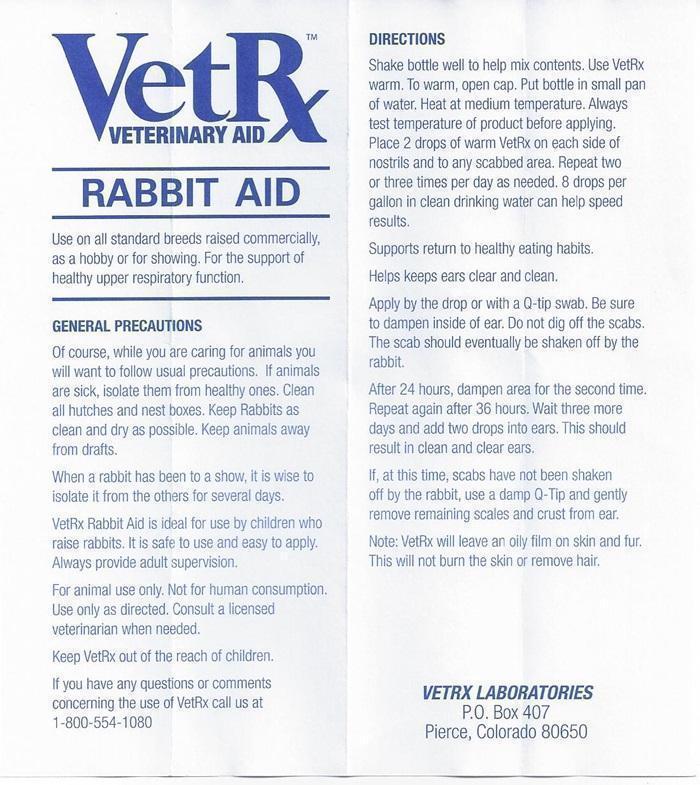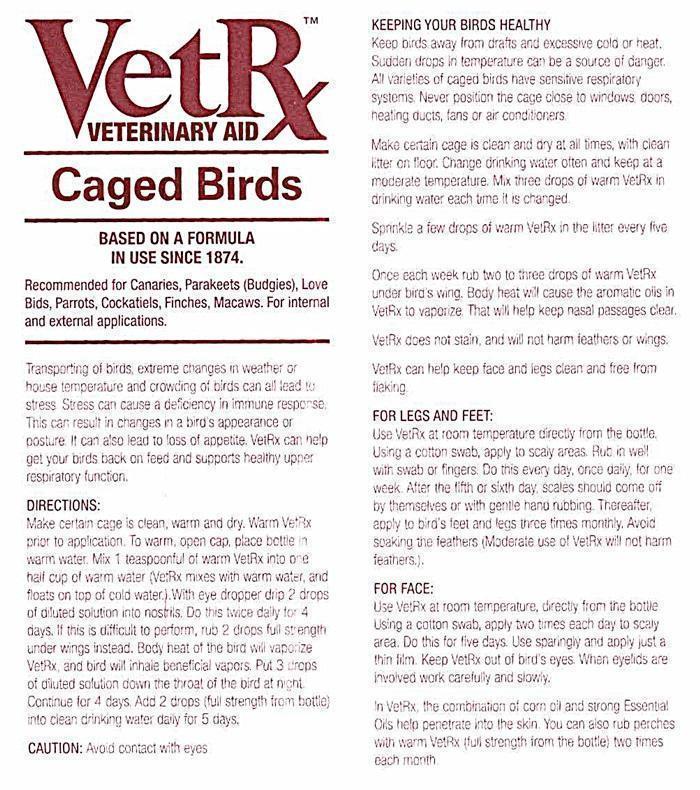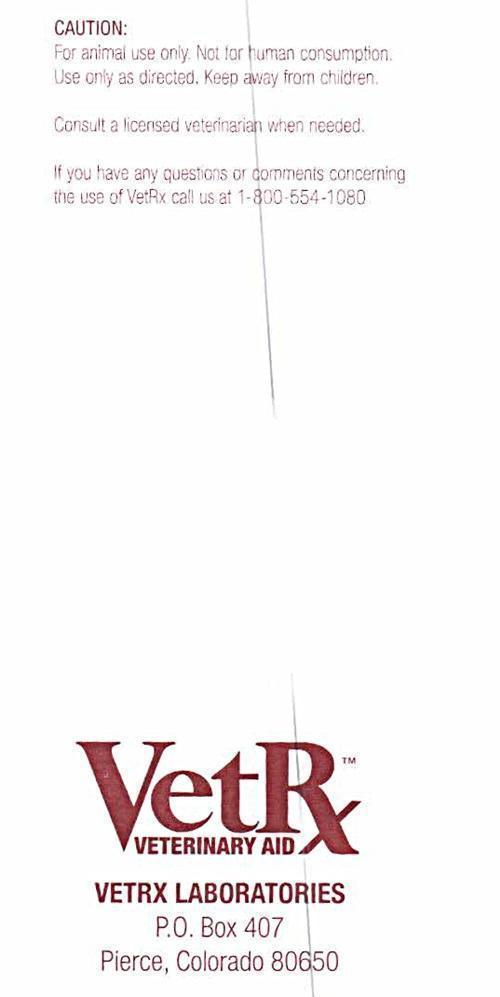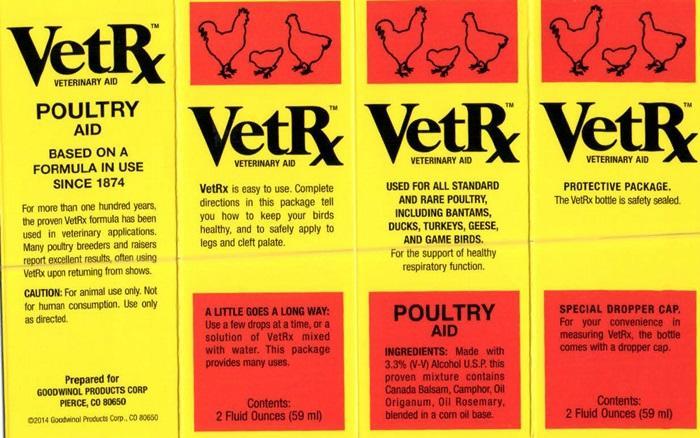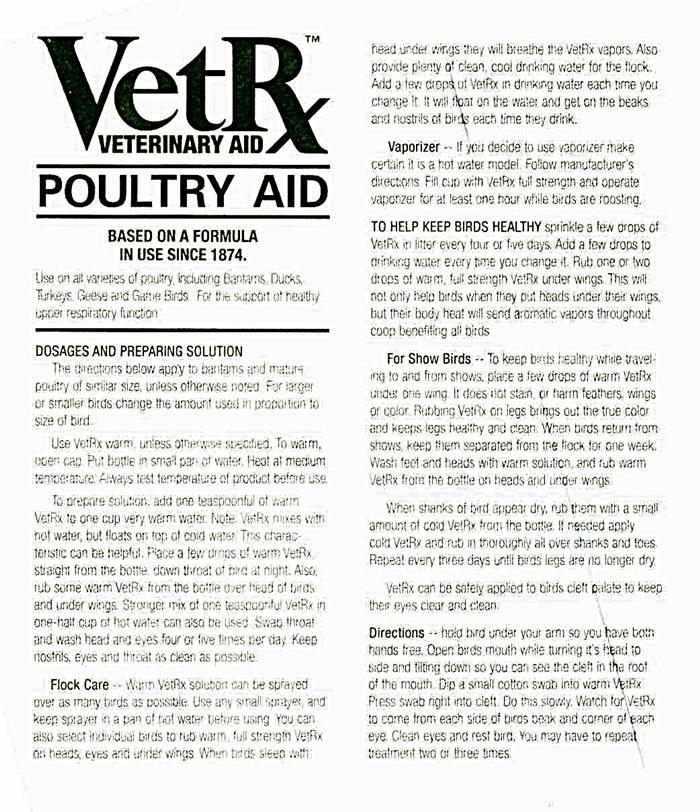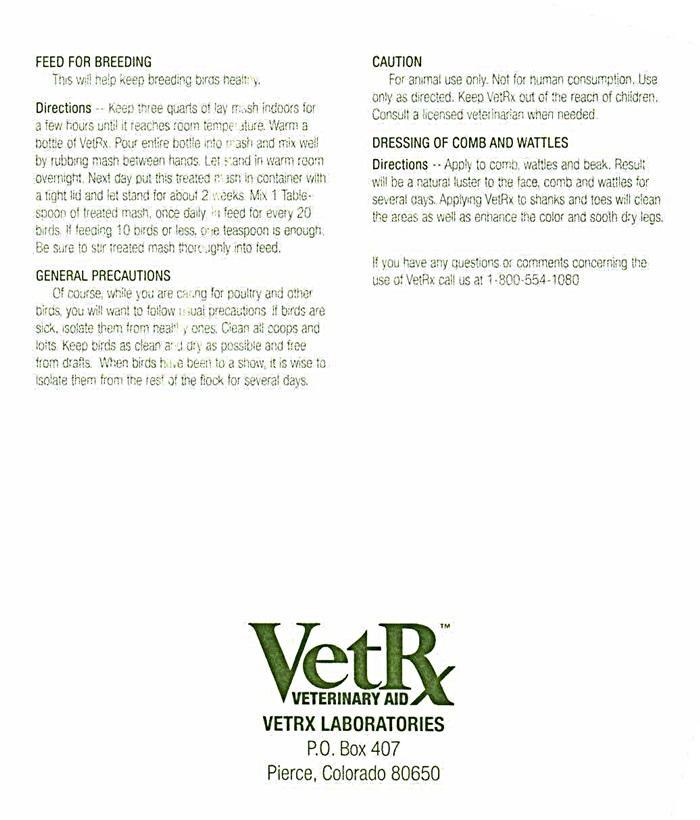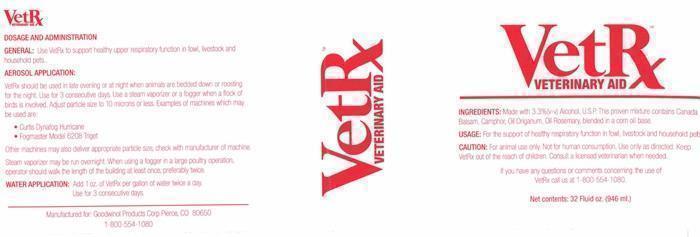 DRUG LABEL: VetRx Veterinary Aid
NDC: 59947-122 | Form: LIQUID
Manufacturer: VetRx Labs
Category: animal | Type: OTC ANIMAL DRUG LABEL
Date: 20250925

ACTIVE INGREDIENTS: ALCOHOL 3.3 mg/100 mL; CAMPHOR (SYNTHETIC) 2.0 mg/100 mL
INACTIVE INGREDIENTS: ORIGANUM OIL; ROSEMARY OIL; CORN OIL; CANADA BALSAM

INGREDIENTS:

Made with 3.3% (v-v) Alcohol, U.S.P. This proven mixture conntains Canada Balsam, Camphor, Oil Origanum, Oil Rosemary, blended in a corn base.

USAGE:

For the support of healthy respiratory function in fowl, livestock and household pets.

CAUTION:

For animal use only. Not for human consumption. Use only as directed. Keep VetRx out of the reach of children. Consult a licensed veterinarian when needed.

DOSAGE AND ADMINISTRATION GENERAL: AEROSOL APPLICATION: WATER APPLICATION:

GENERAL: Use VetRx to support healthy upper respiratory function in fowl, livestock and household pets.

AEROSOL APPLICATION:

VetRx should be used in the evening or at night when animals are bedded down or roosting for the night. Use for 3 consecutive days. Use a steam vaporizer or a fogger when a flock of birds is involved. Adjust particle size to 10 microns or less. Examples of machines which may be used are:

- Curtis Dynafog Hurricanne
- Fogmaster Model 6208 Triget

Other machines may also deliver appropriate particle size, check with manufacture of machine.

Steam vaporizers may be run overnight. When using a fogger in a large poultry operation, operator should walk the length of the building at least once, preferably twice.

WATER APPLICATION: Add 1 oz. of VetRx per gallon of water twice a day.

Use for 3 consecutive days.

QUESTIONS OR COMMENTS

If you have any questions or comments concerning the use of VetRx call us at 1-800-554-1080

VetRx Product Label

VetRx

VETERINARY AID

Manufactured for: Goodwinol Products Corp Pierce, CO 80650

1-800-554-1080

Net contents: 32 Fluid oz. (946 ml.)

res

VetRx™ EQUINE FORMULA

VetRx

VETERINARY AID

EQUINE FORMULA

Net contents: 32 fluid oz.. (948 ml.)

VetRx

VETERINARY AID

Manufactured for: Goodwinol Products Corp Pierce, CO 80650

1-800-554-1080

res

VetRx™ CAGED BIRD REMEDY

VetRx™ VETERINARY REMEDY
CAGED BIRD REMEDY
BASED ON A FORMULA IN USE SINCE 1874

For more than 100 years, the proven VetRx formula has been used as a remedy in veterinary applications. Many bird pet owners report excellent results in controling respiratory ailments, scaly-face and scaly-leg mite problems in their birds.

Prepared for GOODWINOL PRODUCTS CORP
PIERCE,CO 80650

©2011 Goodwinol Products Corp. CO 80650

VetRx CAGED BIRD REMEDY

is easy to use. Complete directions in this package tell you how to control respiratory ailments in your birds, and how to treat individual birde for scaly-face and scaly-leg mites.

A LITTLE GOES A LONG WAY.

Most treatments use a few drops at a time, or recommend a solution of VetRx mixed with water, so this package provides many treatments.

Contains: 2 Fluid Ounces (59 ml)

FOR CANARIES • PARAKEETS • LOVE BIRDS • PARROTS • COCKATIELS • FINCHES • MACAWS

INGREDIENTS: Made with 3.3% (v-v) Alcohol U.S.P.. This proven mixture contains Canada Balsam, Camphor OilOriganum, Oil Rosemary, blended in a corn oil base.

PROTECTIVE PACKAGE.

The VetRx bottle is safety sealed.

SPECIAL DROPPER CAP.

For your convenience in measuring VetRx the bottle comes with a dropper cap.

VetRx™

VETERINARY AID
VETRX LABORATORIES
P.O. Box 407

Pierce, Colorado 80650

res

VetRx VETERINARY AID RABBIT AID Label

VetRx™ VETERINARY AID

RABBIT AID

BASED ON A FORMULA IN USE SINCE 1874

For more than 100 years, the proven VetRx formula has been used in veterinary applications. Many rabbit breeders and raisers report excellent results, often using VetRx upon returning from shows.

VetRx is easy to use. Complete directions in this package tell you how to keep your rabbits healthy and their ears clean.

A LITTLE GOES A LONG WAY:

Use a few drops at a time, or a solution of VetRx mixed with water. This package provides many uses

Contents

2 Fluid Ounces (59 ml)

PROTECTIVE PACKAGE.

The VetRx bottle is safety sealed.

SPECIAL DROPPER CAP.

For your convience in measuring VetRx the bottle comes with a dropper cap.

Prepared for

GOODWINOL PRODUCTS CORP
PIERCE, CO 80650

©2014 Goodwinol Products Corp., CO 80650

VETRX LABORATORIES

P.O. Box 407

Pierce, Colorado 80650

res

VetRx VETERINARY AID POULTRY AID label

VetRx™ VETERINARY AID

POULTRY AID

BASED ON A FORMULA IN USE SINCE 1874

For more than 100 years, the proven VetRx formula has been used in veterinary applications. Many poultry breeders and raisers report excellent results, often using VetRx upon returning from shows.

VetRx is easy to use. Complete directions in this package tell you how to keep your birds healthy and to safely apply to legs and cleft palate.

A LITTLE GOES A LONG WAY:

Use a few drops at a time, or a solution of VetRx mixed with water. This package provides many uses

Contents

2 Fluid Ounces (59 ml)

PROTECTIVE PACKAGE.

The VetRx bottle is safety sealed.

SPECIAL DROPPER CAP.

For your convience in measuring VetRx the bottle comes with a dropper cap.

Prepared for

GOODWINOL PRODUCTS CORP
PIERCE, CO 80650

©2014 Goodwinol Products Corp., CO 80650

VETRX LABORATORIES

P.O. Box 407

Pierce, Colorado 80650